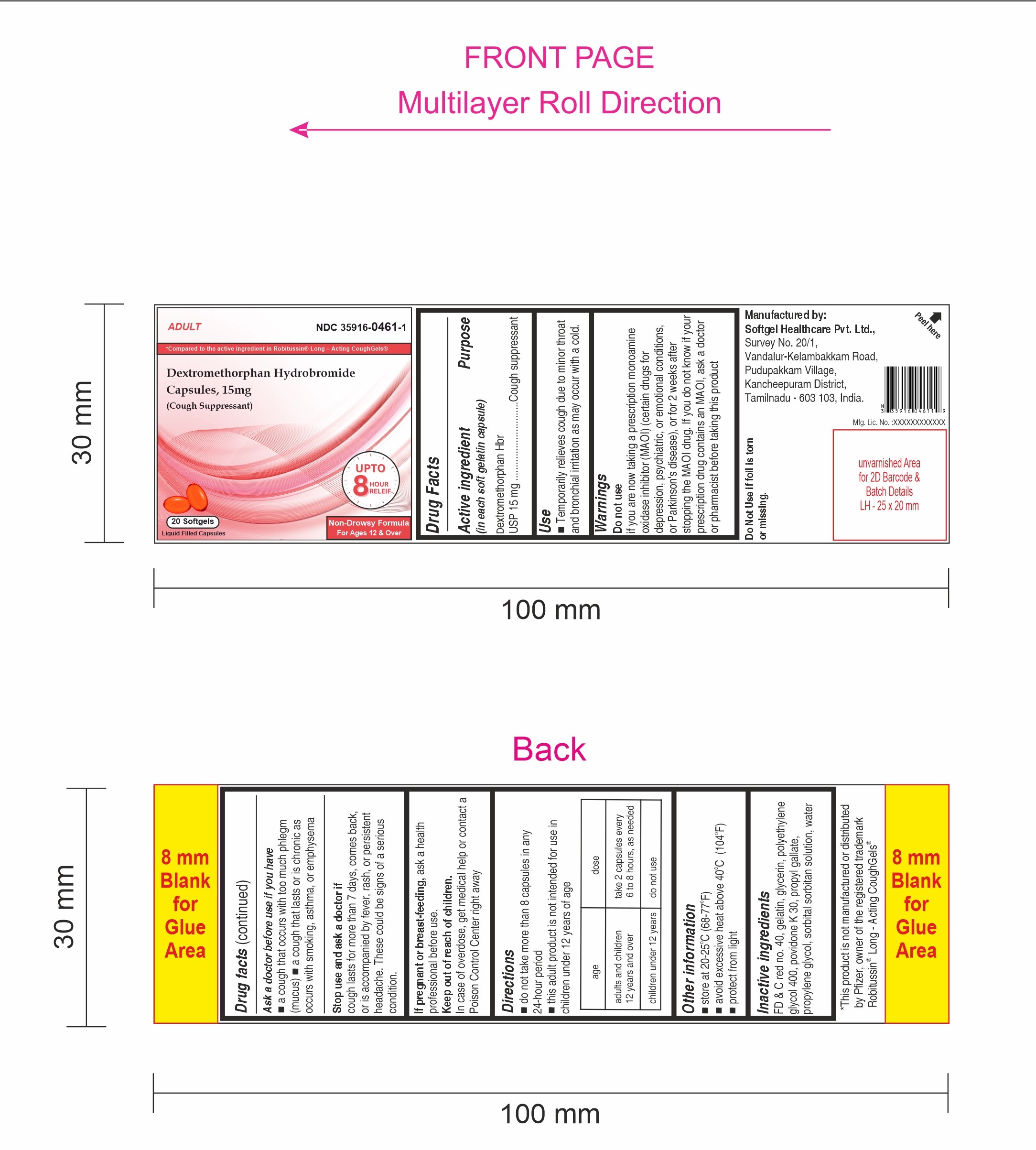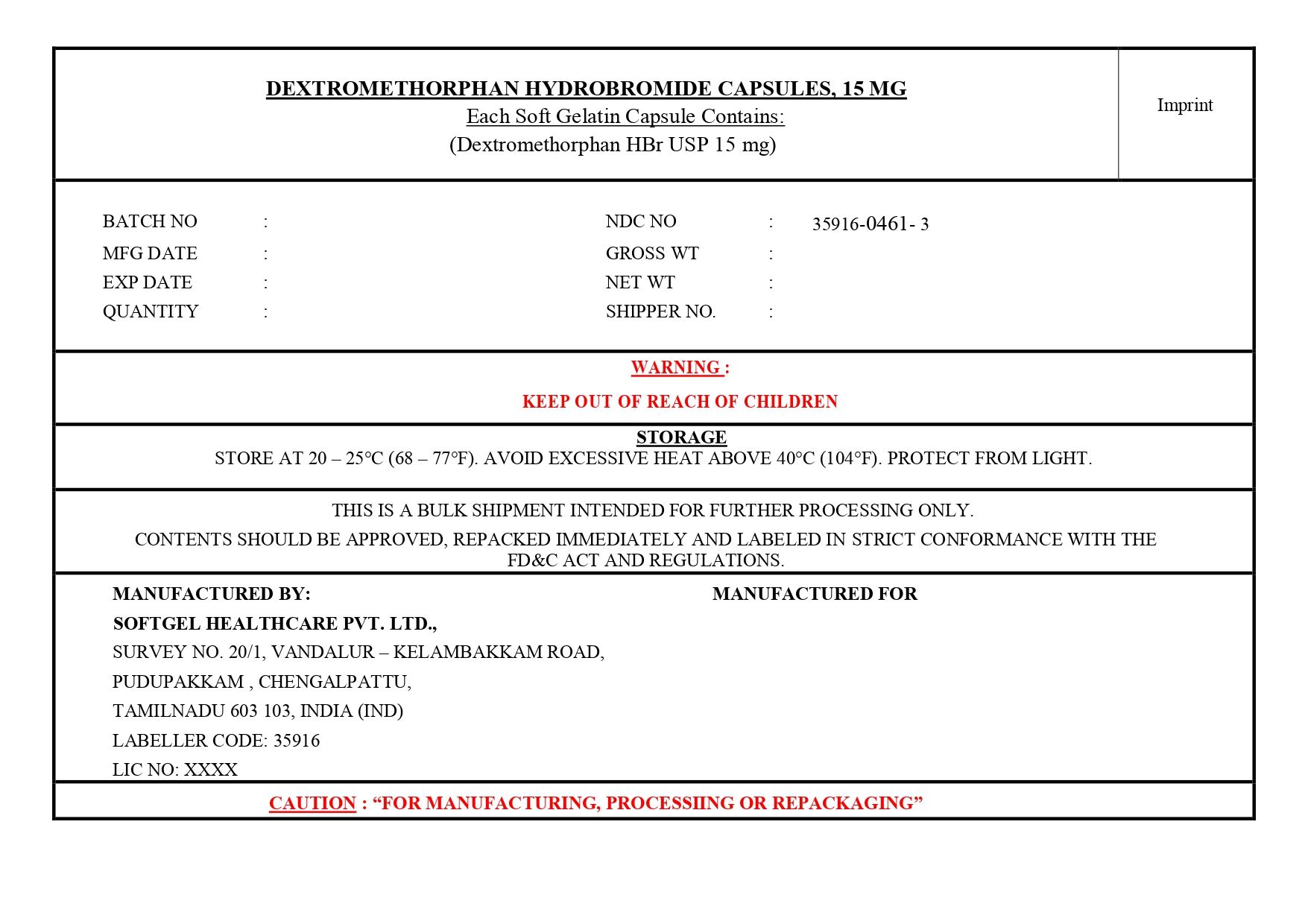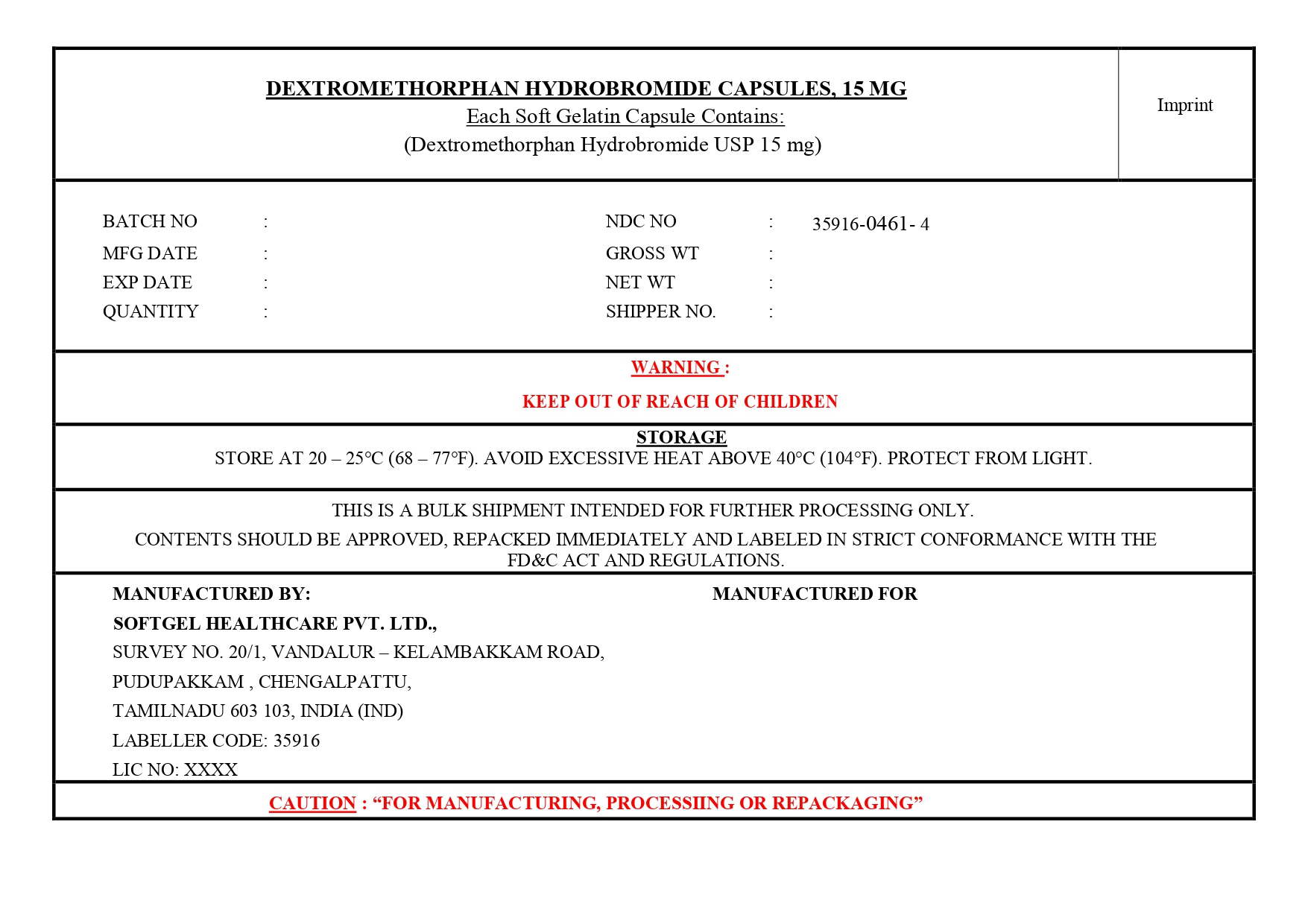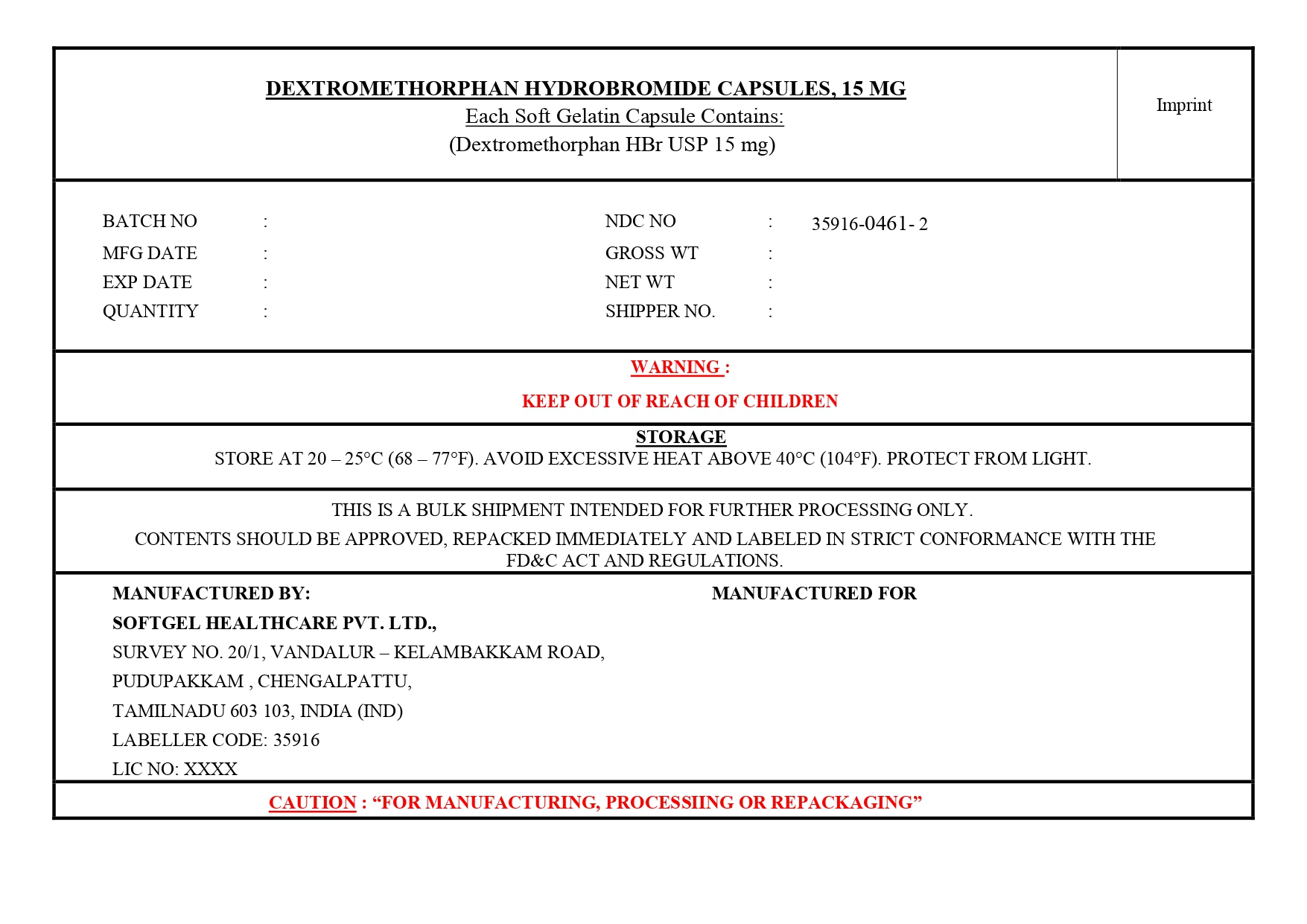 DRUG LABEL: Dextromethorphan Hydrobromide
NDC: 35916-0461 | Form: CAPSULE, LIQUID FILLED
Manufacturer: Softgel Healthcare Pvt Ltd
Category: otc | Type: HUMAN OTC DRUG LABEL
Date: 20260112

ACTIVE INGREDIENTS: DEXTROMETHORPHAN HYDROBROMIDE 15 mg/1 1
INACTIVE INGREDIENTS: GLYCERIN; GELATIN, UNSPECIFIED; FD&C RED NO. 40; PROPYL GALLATE; WATER; SORBITOL; PROPYLENE GLYCOL; POVIDONE K30; POLYETHYLENE GLYCOL 400

Dextromethorphan Hydrobromide Capsules, 15mg

Active ingredient (in each soft gelatin capsule)

Dextromethorphan HBr, USP 15 mg

Purpose

Cough suppressant

Use

temporarily relieves cough due to minor throat and bronchial irritation as may occur with a cold.

Warnings

Do not use if you are now taking a prescription monoamine oxidase inhibitor (MAOI) (certain drugs for depression, psychiatric, or emotional conditions, or Parkinson's disease), or for 2 weeks after stopping the MAOI drug. If you do not know if your prescription drug contains an MAOI, ask a doctor or pharmacist before taking this product.

Ask a doctor before use if you have

- a cough that occurs with too much phlegm (mucus)
- a cough that lasts or is chronic as occurs with smoking, asthma, or emphysema

Stop use and ask a doctor if cough lasts for more than 7 days, comes back, or is accompanied by fever, rash, or persistent headache. These could be signs of a serious condition.

PREGNANCY OR BREAST FEEDING

If pregnant or breast-feeding, ask a health professional before use.

Keep out of reach of children. In case of overdose, get medical help or contact a Poison Control Center right away.

Directions

- do not take more than 8 capsules in any 24-hour period
- this adult product is not intended for use in children under 12 years of age

age | dose
adults and children 12 years and over | take 2 capsules every 6 to 8 hours, as needed
children under 12 years | do not use

Other information

- store at 20-25°C (68-77°F)
- avoid excessive heat above 40°C (104°F)
- protect from light

Inactive ingredients

FD & C Red no. 40, gelatin, glycerin, polyethylene glycol 400, povidone K 30, propyl gallate, propylene glycol, purified water, sorbital sorbitan solution

Manufactured By

Softgel Healthcare Pvt. Ltd.,

Survey No. 20/1, Vandalur-Kelambakkam Road,

Pudupakkam , chengalpattu district,

Tamilnadu - 603 103, India.

Mfg. Lic. No.:XXXXXXXXXXXX